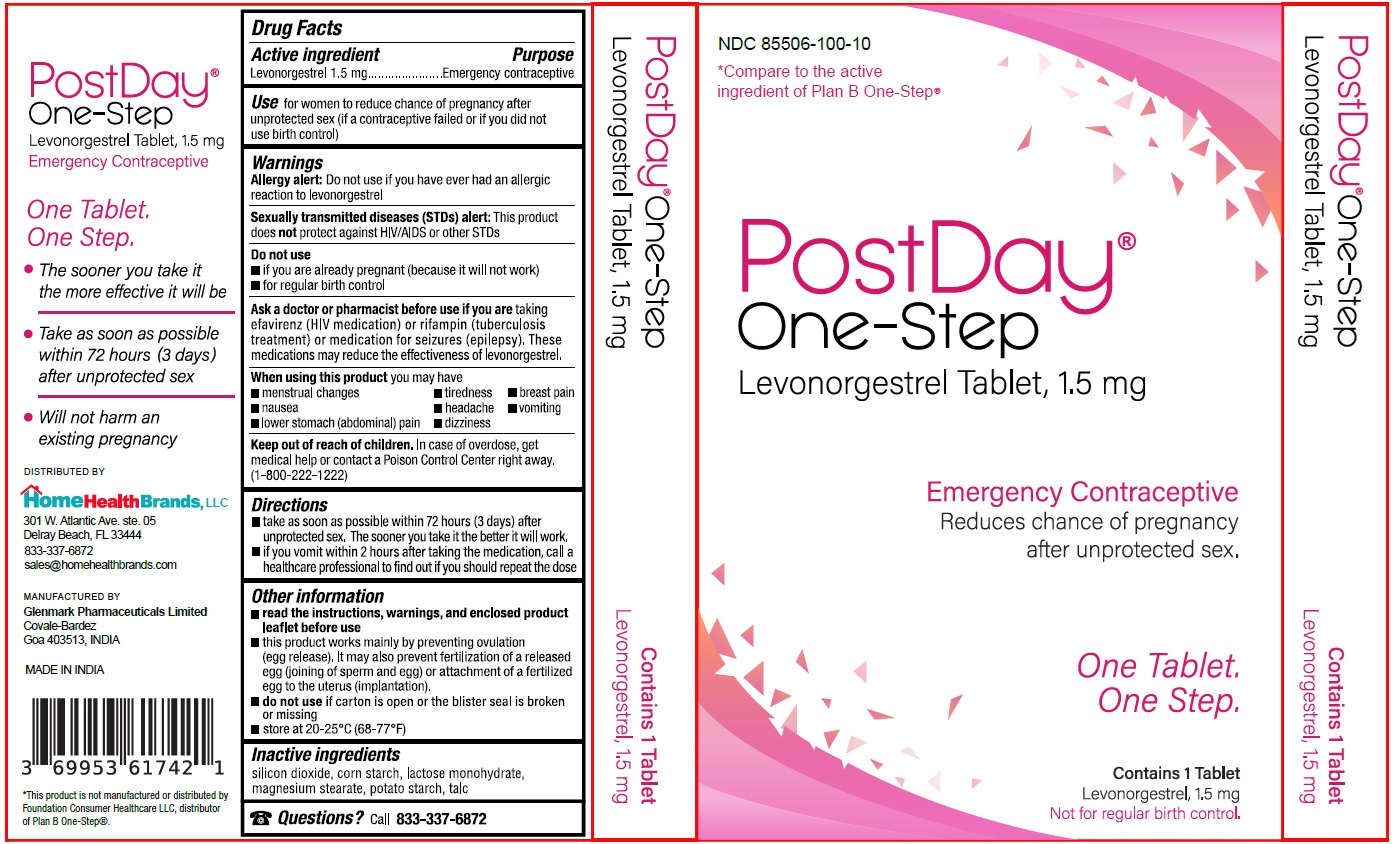 DRUG LABEL: PostDay One-Step
NDC: 85506-100 | Form: TABLET
Manufacturer: Home Health Brands, LLC
Category: otc | Type: HUMAN OTC DRUG LABEL
Date: 20250423

ACTIVE INGREDIENTS: LEVONORGESTREL 1.5 mg/1 1
INACTIVE INGREDIENTS: SILICON DIOXIDE; STARCH, CORN; LACTOSE MONOHYDRATE; MAGNESIUM STEARATE; STARCH, POTATO; TALC

PostDay® One-Step

Active ingredient

Levonorgestrel 1.5 mg

Purpose

Emergency contraceptive

Use

for women to reduce chance of pregnancy after unprotected sex (if a contraceptive failed or if you did not use birth control)

Warnings

Allergy alert: Do not use if you have ever had an allergic reaction to levonorgestrel

Sexually transmitted diseases (STDs) alert: This product does not protect against HIV/AIDS or other STDs

Do not use
• if you are already pregnant (because it will not work)
• for regular birth control

Ask a doctor or pharmacist before use if you are taking efavirenz (HIV medication) or rifampin (tuberculosis treatment) or medication for seizures (epilepsy). These medications may reduce the effectiveness of levonorgestrel.

When using this product you may have
• menstrual changes • tiredness • breast pain
• nausea • headache • vomiting
• lower stomach (abdominal) pain • dizziness

Keep out of reach of children. In case of overdose, get medical help or contact a Poison Control Center right away. (1-800-222-1222)

Directions

• take as soon as possible within 72 hours (3 days) after unprotected sex. The sooner you take it the better it will work.
• if you vomit within 2 hours after taking the medication, call a healthcare professional to find out if you should repeat the dose

Other information

• read the instructions, warnings, and enclosed product leaflet before use
• this product works mainly by preventing ovulation (egg release). It may also prevent fertilization of a released egg (joining of sperm and egg) or attachment of a fertilized egg to the uterus (implantation).
• do not use if carton is open or the blister seal is broken or missing
• store at 20-25°C (68° to 77°F)

Inactive ingredients

silicon dioxide, corn starch, lactose monohydrate, magnesium stearate, potato starch, talc

Questions?

Call 833-337-6872

*Compare to the active ingredient of Plan B One-Step®

One Tablet. One Step.

Not for regular birth control.

• The sooner you take it the more effective it will be
• Take as soon as possible within 72 hours (3 days) after unprotected sex
• Will not harm an existing pregnancy

DISTRIBUTED BY
HomeHealthBrands, LLC
301 W. Atlantic Ave. ste. 05
Delray Beach, FL 33444
833-337-6872
sales@homehealthbrands.com

MANUFACTURED BY
Glenmark Pharmaceuticals Limited
Covale-Bardez
Goa 403515, INDIA

MADE IN INDIA

*This product is not manufactured or distributed by Foundation Consumer Healthcare LLC, distributor of Plan B One-Step®.